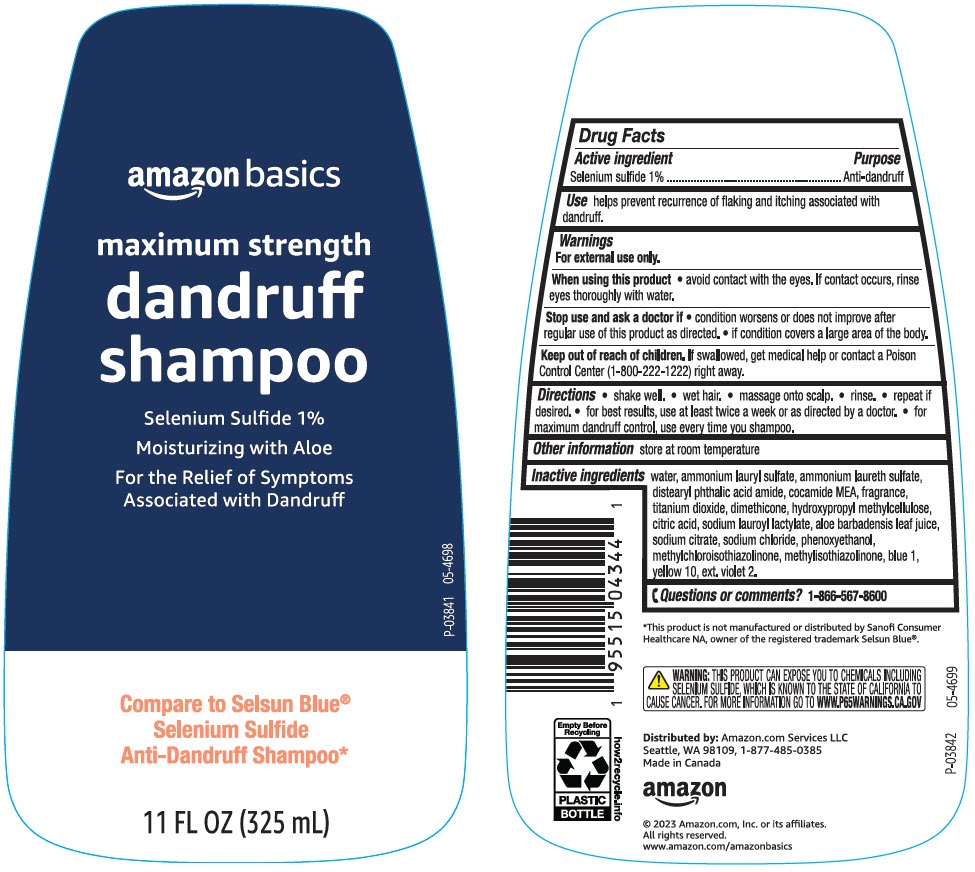 DRUG LABEL: amazon basics maximum strength dandruff
NDC: 72288-551 | Form: SHAMPOO
Manufacturer: AMAZON.COM SERVICES LLC
Category: otc | Type: HUMAN OTC DRUG LABEL
Date: 20240226

ACTIVE INGREDIENTS: Selenium sulfide 10 mg/1 mL
INACTIVE INGREDIENTS: Water; Ammonium Lauryl Sulfate; Ammonium Laureth-5 Sulfate; Distearyl Phthalamic Acid; Coco Monoethanolamide; Titanium Dioxide; Dimethicone; Hypromellose, Unspecified; Citric Acid Monohydrate; Sodium Lauroyl Lactylate; Aloe Vera Leaf; Sodium Citrate, Unspecified Form; Sodium Chloride; Phenoxyethanol; Methylchloroisothiazolinone; Methylisothiazolinone; Fd&C Blue No. 1; D&C Yellow No. 10; Ext. D&C Violet No. 2

amazon basics maximum strength dandruff shampoo
Anti-dandruff

Drug Facts

Active ingredient

Selenium sulfide 1%

Purpose

Anti-dandruff

Use

helps prevent recurrence of flaking and itching associated with dandruff.

Warnings

For external use only.

Ask a doctor before using this product if condition covers a large area of the body.

When using this product

- avoid contact with the eyes. If contact occurs, rinse eyes thoroughly with water.

Stop use and ask a doctor if

- condition worsens or does not improve after regular use of this product as directed.
- if condition covers a large area of the body.

Keep out of reach of children. If swallowed, get medical help or contact a Poison Control Center (1-800-222-1222) right away.

Directions

- shake well.
- wet hair.
- massage onto scalp.
- rinse.
- repeat if desired.
- for best results, use at least twice a week or as directed by a doctor.
- for maximum dandruff control, use every time you shampoo.

Other information

- store at room temperature

Inactive ingredients

water, ammonium lauryl sulfate, ammonium laureth sulfate, distearyl phthalic acid amide, cocamide MEA, fragrance, titanium dioxide, dimethicone, hydroxypropyl methylcellulose, citric acid, sodium lauroyl lactylate, aloe barbadensis leaf juice, sodium citrate, sodium chloride, phenoxyethanol, methylchloroisothiazolinone, methylisothiazolinone, blue 1, yellow 10, ext. violet 2.

Questions or comments?

1-866-567-8600

Distributed by: Amazon.com Services LLC
Seattle, WA 98109, 1-877-485-0385

PRINCIPAL DISPLAY PANEL - 325 mL Bottle Label

amazon basics

maximum strength

dandruff
shampoo

Selenium Sulfide 1%
Moisturizing with Aloe
For the Relief of Symptoms
Associated with Dandruff

Compare to Selsun Blue®
Selenium Sulfide
Anti-Dandruff Shampoo*

11 FL OZ (325 mL)

P-03841
05-4698